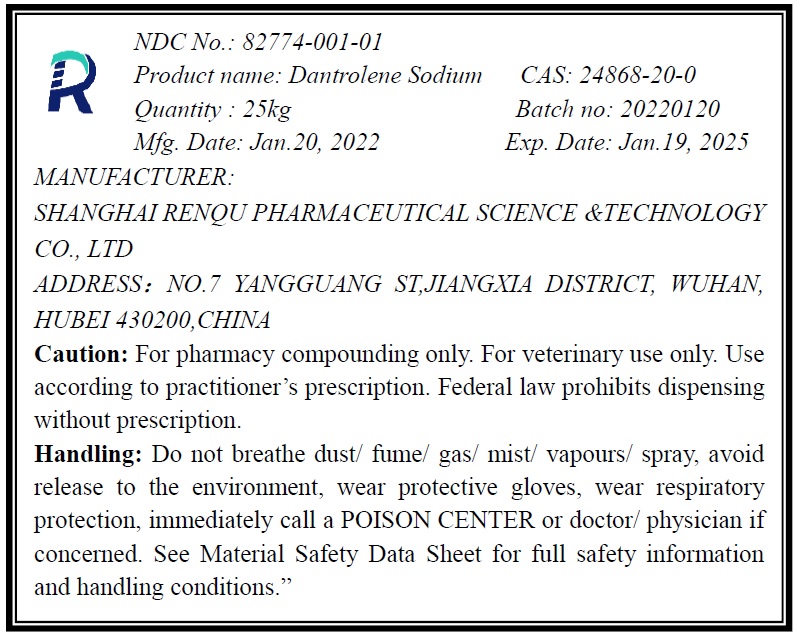 DRUG LABEL: Dantrolene Sodium
NDC: 82774-001 | Form: POWDER
Manufacturer: Shanghai Renqu Pharmaceutical Science & Technology Co., Ltd.
Category: other | Type: BULK INGREDIENT - ANIMAL DRUG
Date: 20220618

ACTIVE INGREDIENTS: DANTROLENE SODIUM 1 kg/1 kg

Dantrolene Sodium